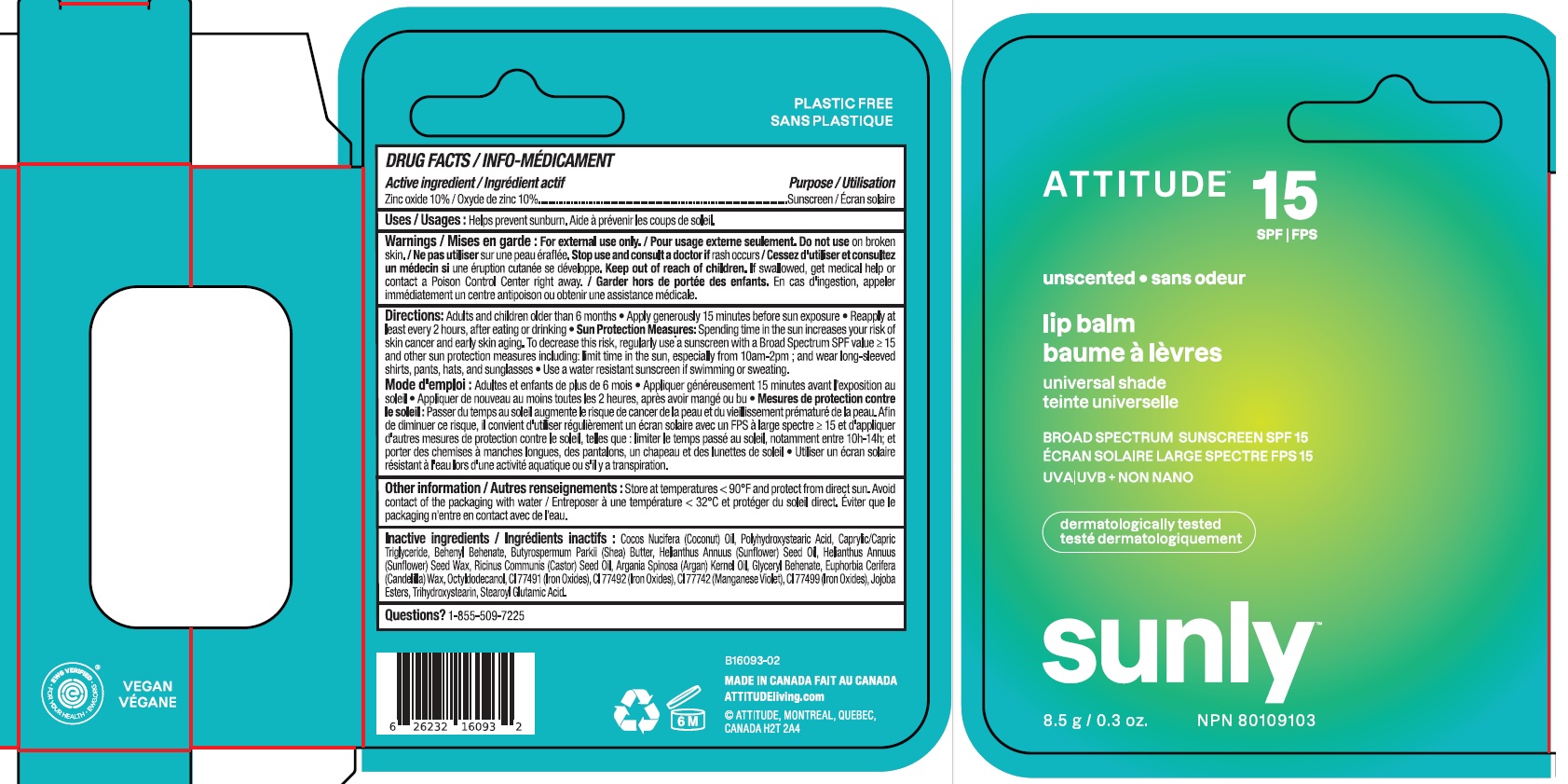 DRUG LABEL: ATTITUDE Sunly Lip balm Unscented SPF 15
NDC: 61649-093 | Form: STICK
Manufacturer: 9055-7588 Quebec Inc. DBA Attitude
Category: otc | Type: HUMAN OTC DRUG LABEL
Date: 20251203

ACTIVE INGREDIENTS: ZINC OXIDE 10 g/100 g
INACTIVE INGREDIENTS: MANGANESE VIOLET; STEAROYL GLUTAMIC ACID; FERRIC OXIDE RED; HELIANTHUS ANNUUS SEED WAX; GLYCERYL MONOBEHENATE; FERRIC OXIDE YELLOW; ARGAN OIL; CASTOR OIL; CANDELILLA WAX; OCTYLDODECANOL; JOJOBA OIL; COCONUT OIL; POLYHYDROXYSTEARIC ACID (2300 MW); FERROSOFERRIC OXIDE; MEDIUM-CHAIN TRIGLYCERIDES; SHEA BUTTER; BEHENYL BEHENATE; SUNFLOWER OIL; TRIHYDROXYSTEARIN

ATTITUDE Sunly Lip balm - Unscented - SPF 15

DRUG FACTS

ACTIVE INGREDIENT

Zinc oxide (10 %)

PURPOSE

Sunscreen

INDICATIONS AND USAGE

Helps prevent sunburn.

WARNINGS

For external use only.

Do not use on broken skin.

Keep out of reach of children. If swallowed, get medical help or contact a Poison Control Center right away.

Stop use and consult a doctor if rash occurs.

DOSAGE AND ADMINISTRATION

Adults and children older than 6 months.

- Apply generously 15 minutes before sun exposure.
- Reapply at least every 2 hours, after eating or drinking.
- Sun Protection Measures: Spending time in the sun increases your risk of skin cancer and early aging. To decrease this risk, regularly use a sunscreen with a Broad Spectrum SPFvalue of 15 or higher and other sun protection measures including: limit time in the sun, especially from 10am-2pm; and wear long-sleeved shirts, pants, hats and sunglasses.
- Use a water resistant sunscreen if swimming or sweating.

STORAGE AND HANDLING

Store at temperatures < 90F and protect from direct sun. Avoid contact of packaging with water.

INACTIVE INGREDIENT

Cocos Nucifera (Coconut) Oil, Polyhydroxystearic Acid, Caprylic/Capric Triglyceride, Behenyl Behenate, Butyrospermum Parkii (Shea) Butter, Helianthus Annuus (Sunflower) Seed Oil, Helianthus Annuus (Sunflower) Seed Wax, Ricinus Communis (Castor) Seed Oil, Argania Spinosa (Argan) Kernel Oil, Glyceryl Behenate, Euphorbia Cerifera (Candelilla) Wax, Octyldodecanol, CI 77491 (Iron Oxides), CI 77492 (Iron Oxides), CI 77742 (Manganese Violet), CI 77499 (Iron Oxides), Jojoba Esters, Trihydroxystearin, Stearoyl Glutamic Acid.

Questions ? 1-855-509-7225

PACKAGE LABEL

ATTITUDE

SPF 15

unscented

lip balm

universal shade

BROAD SPECTRUM SUNSCREEN SPF 15

UVA UVB + NON NANO

SUNLY Plastic Free Suncare

8.5 g / 0.3 oz.

NPN 80109103

Vegan

EWG Verified

Dermatologically tested